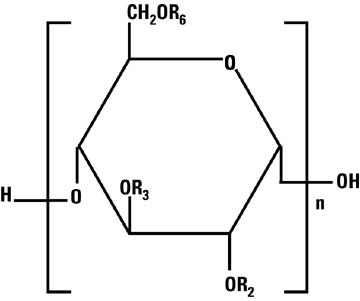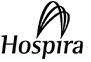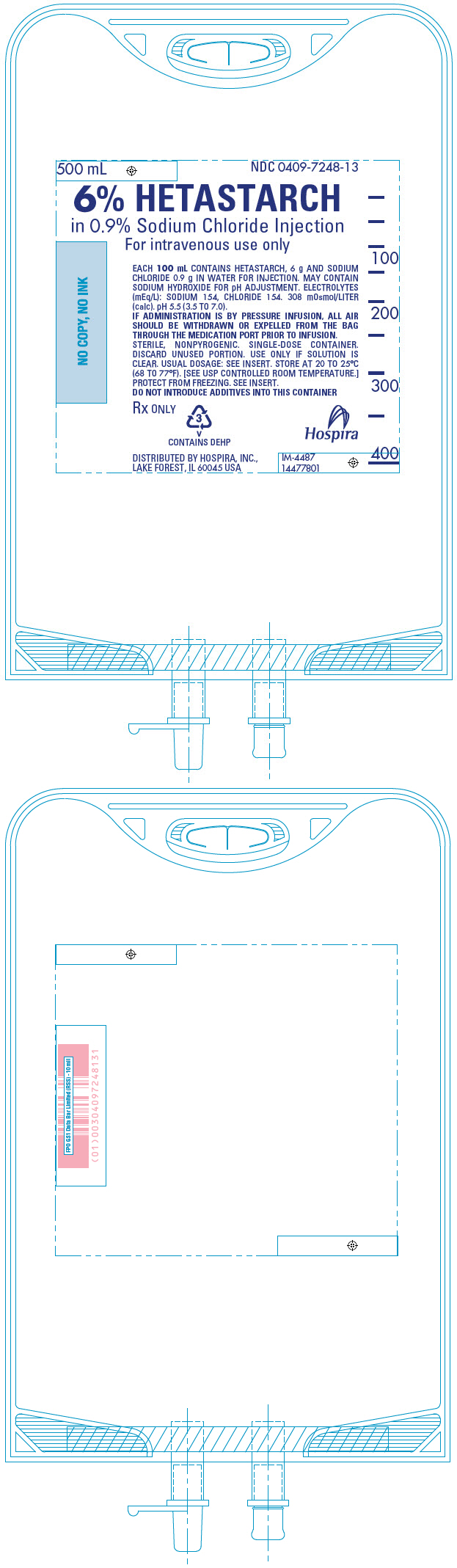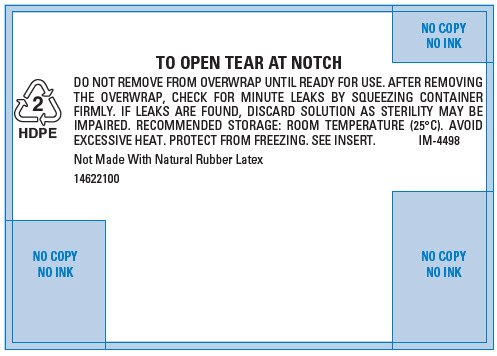 DRUG LABEL: Hetastarch in Sodium Chloride
NDC: 0409-7248 | Form: INJECTION, SOLUTION
Manufacturer: Hospira, Inc.
Category: prescription | Type: HUMAN PRESCRIPTION DRUG LABEL
Date: 20250929

ACTIVE INGREDIENTS: HETASTARCH 6 g/100 mL
INACTIVE INGREDIENTS: SODIUM CHLORIDE 0.9 g/100 mL; WATER; SODIUM HYDROXIDE

HIGHLIGHTS OF PRESCRIBING INFORMATION

These highlights do not include all the information needed to use 6% Hetastarch in 0.9% Sodium Chloride Injection safely and effectively. See full prescribing information for 6% Hetastarch in 0.9% Sodium Chloride Injection.
6% Hetastarch in 0.9% Sodium Chloride Injection, for intravenous use
Initial U.S. Approval: 1991

WARNING: MORTALITY; KIDNEY INJURY; COAGULOPATHY

WARNING: MORTALITY;
KIDNEY INJURY; COAGULOPATHY

See full prescribing information for complete boxed warning.

- Use of hydroxyethyl starch (HES) products, including 6% Hetastarch in 0.9% Sodium Chloride Injection, increases risk of
  - Mortality
  - Kidney injury (5.1)
  - Coagulopathy (5.2)
- DO NOT use HES products, including 6% Hetastarch in 0.9% Sodium Chloride Injection, unless adequate alternative treatment is unavailable. (1)

1 INDICATIONS AND USAGE

- 6% Hetastarch in 0.9% Sodium Chloride Injection is a hetastarch indicated for treatment of hypovolemia when plasma volume expansion is desired in settings where adequate alternative treatment is unavailable. (1)
- 6% Hetastarch in 0.9% Sodium Chloride Injection in leukapheresis has shown to be safe and efficacious in improving the harvesting and increasing the yield of granulocytes by centrifugal means. (1)

2 DOSAGE AND ADMINISTRATION

For intravenous use only.

Recommended Dosage
 | Dose
Adults (2.1) | 500 to 1000 mL
Leukapheresis (2.2) | 250 to 700 mL of 6% Hetastarch in 0.9% Sodium Chloride Injection with citrate anticoagulant is added to the input line of the centrifugation apparatus.

3 DOSAGE FORMS AND STRENGTHS

- 30 g hetastarch in 500 mL 0.9% sodium chloride injection. (3)

4 CONTRAINDICATIONS

- Do not use HES products, including 6% Hetastarch in 0.9% Sodium Chloride Injection, unless adequate alternative treatment is unavailable.

5 WARNINGS AND PRECAUTIONS

- Avoid use in patients with pre-existing renal dysfunction (5.1)
- Increased risk of mortality and acute kidney injury (AKI) in critically ill patients, including patients with sepsis; surgical patients; and blunt trauma patients (5.1)
- Discontinue use of 6% Hetastarch in 0.9% Sodium Chloride Injection at the first sign of renal injury (5.1)
- Continue to monitor renal function for at least 90 days as use of RRT has been reported up to 90 days after administration of HES products, including 6% Hetastarch in 0.9% Sodium Chloride Injection (5.1)
- 6% Hetastarch in 0.9% Sodium Chloride Injection is not recommended for use as a cardiac bypass pump prime, while the patient is on cardiopulmonary bypass, or in the immediate period after the pump has been discontinued because of the risk of increasing coagulation abnormalities and bleeding in patients whose coagulation status is already impaired. Discontinue use of 6% Hetastarch in 0.9% Sodium Chloride Injection at first sign of coagulopathy (5.2)
- Monitor liver function in patients receiving HES products, including 6% Hetastarch in 0.9% Sodium Chloride Injection (5.2)

6 ADVERSE REACTIONS

- Most common adverse reactions are hypersensitivity, coagulopathy, hemodilution, circulatory overload and metabolic acidosis. (6.2)

To report SUSPECTED ADVERSE REACTIONS, contact Hospira, Inc. at 1-800-441-4100 or FDA at 1-800-FDA-1088 or www.fda.gov/medwatch.

7 DRUG INTERACTIONS

- Use with caution with drugs that negatively influence the coagulation system. (7)
- The safety and compatibility of other additives have not been established. (7)

FULL PRESCRIBING INFORMATION

WARNING: MORTALITY; KIDNEY INJURY; COAGULOPATHY

- Use of hydroxyethyl starch (HES) products, including 6% Hetastarch in 0.9% Sodium Chloride Injection, increases risk of
  - Mortality
  - Kidney injury (5.1)
  - Coagulopathy (5.2)
- DO NOT use HES products, including 6% Hetastarch in 0.9% Sodium Chloride Injection, unless adequate alternative treatment is unavailable. (1)

1 INDICATIONS AND USAGE

6% Hetastarch in 0.9% Sodium Chloride Injection is indicated in the treatment of hypovolemia when plasma volume expansion is desired in settings where adequate alternative treatment is unavailable. It is not a substitute for blood or plasma.

The adjunctive use of 6% Hetastarch in 0.9% Sodium Chloride Injection in leukapheresis has also been shown to be safe and efficacious in improving the harvesting and increasing the yield of granulocytes by centrifugal means.

2 DOSAGE AND ADMINISTRATION

Dosage for Acute Use in Plasma Volume Expansion

6% Hetastarch in 0.9% Sodium Chloride Injection is administered by intravenous infusion only. Total dosage and rate of infusion depend upon the amount of blood or plasma lost and the resultant hemoconcentration.

2.1 Adults

The amount usually administered is 500 to 1000 mL. Doses of more than 1500 mL per day for the typical 70 kg patient (approximately 20 mL per kg of body weight) are usually not required. Higher doses have been reported in postoperative and trauma patients where severe blood loss has occurred [see Warnings and Precautions (5)].

2.2 Leukapheresis

250 to 700 mL of 6% Hetastarch in 0.9% Sodium Chloride Injection with citrate anticoagulant is administered by aseptic addition to the input line of the centrifugation apparatus at a ratio of 1:8 to 1:13 to venous whole blood. The 6% Hetastarch in 0.9% Sodium Chloride Injection and citrate should be thoroughly mixed to assure effective anticoagulation of blood as it flows through the leukapheresis machine.

2.3 Direction for use for 6% Hetastarch in 0.9% Sodium Chloride Injection

- Do not use plastic container in series connection. If administration is controlled by a pumping device, care must be taken to discontinue pumping action before the container runs dry or air embolism may result. If administration is not controlled by a pumping device, refrain from applying excessive pressure (>300mmHg) causing distortion to the container such as wringing or twisting. Such handling could result in breakage of the container.
- Parenteral drug products should be inspected visually for particulate matter and discoloration prior to administration whenever solution and container permit. Use only if solution is clear and container and seals are intact.
- Intended for intravenous administration using sterile equipment. It is recommended that intravenous administration apparatus be replaced at least once every 24 hours.
- Withdraw or expel all air from the bag through the medication port prior to infusion if administration is by pressure infusion.
- For single use only. The solution contains no bacteriostat, antimicrobial agent or added buffers (except for pH adjustment) and is intended only for single-dose injection. When smaller doses are required the unused portion should be discarded.

CAUTION: Before administering to the patient, review these directions:

Visual Inspection

- Do not remove the plastic infusion container from its overwrap until immediately before use.
- Inspect each container. Read the label. Ensure solution is the one ordered and is within the expiration date.
- Invert container and carefully inspect the solution in good light for cloudiness, haze, or particulate matter.
- Any container which is suspect should not be used.

To Open

1. Tear overwrap down at notch and remove solution container.

2. Check for minute leaks by squeezing solution container firmly.

3. If any leaks are found, discard solution as sterility may be impaired.

Preparation for Administration

1. Remove plastic protector from sterile set port at bottom of container.

2. Attach administration set. Refer to complete directions accompanying set.

When stored at room temperature, 6% Hetastarch in 0.9% Sodium Chloride Injection admixtures of 500–560 mL with citrate concentrations up to 2.5% were compatible for 24 hours. The safety and compatibility of additives other than citrate have not been established.

3 DOSAGE FORMS AND STRENGTHS

Single-dose container:

- 30 g hetastarch in 500 mL of 0.9% sodium chloride injection.

4 CONTRAINDICATIONS

Do not use HES products, including 6% Hetastarch in 0.9% Sodium Chloride Injection, unless adequate alternative treatment is unavailable.

5 WARNINGS AND PRECAUTIONS

5.1 Mortality and Renal Dysfunction

- Critically ill patients, including patients with sepsis, are at increased risk of mortality and acute kidney injury (AKI), including need for renal replacement therapy (RRT)
- Surgery patients are at increased risk of mortality and AKI
- Blunt trauma patients are at increased risk of mortality and AKI
- Avoid use in patients with pre-existing renal dysfunction
- Discontinue use of 6% Hetastarch in 0.9% Sodium Chloride Injection at the first sign of renal injury
- Continue to monitor renal function for at least 90 days as use of RRT has been reported up to 90 days after administration of HES products, including 6% Hetastarch in 0.9% Sodium Chloride Injection

5.2 Coagulopathy

- 6% Hetastarch in 0.9% Sodium Chloride Injection is not recommended for use as a cardiac bypass pump prime, while the patient is on cardiopulmonary bypass, or in the immediate period after the pump has been discontinued because of the risk of increasing coagulation abnormalities and bleeding in patients whose coagulation status is already impaired. Monitor the coagulation status of surgery patients, as excess bleeding has been reported with HES solutions in this population. Discontinue use of 6% Hetastarch in 0.9% Sodium Chloride Injection at first sign of coagulopathy^1–2

6% Hetastarch in 0.9% Sodium Chloride Injection has not been adequately evaluated to establish its safety in uses over extended periods other than leukapheresis. 6% Hetastarch in 0.9% Sodium Chloride Injection has been associated with coagulation abnormalities in conjunction with an acquired, reversible von Willebrand's-like syndrome and/or Factor VIII deficiency when used over a period of days. Replacement therapy should be considered if a severe Factor VIII deficiency is identified. If a coagulopathy develops, it may take several days to resolve. Certain conditions may affect the safe use of 6% Hetastarch in 0.9% Sodium Chloride Injection on a chronic basis. For example, in patients with subarachnoid hemorrhage where 6% Hetastarch in 0.9% Sodium Chloride Injection is used repeatedly over a period of days for the prevention of cerebral vasospasm, significant clinical bleeding may occur. Intracranial bleeding resulting in death has been reported.^3

Slight declines in platelet counts and hemoglobin levels have been observed in donors undergoing repeated leukapheresis procedures using 6% Hetastarch in 0.9% Sodium Chloride Injection due to the volume expanding effects of hetastarch and to the collection of platelets and erythrocytes. Hemoglobin levels usually return to normal within 24 hours. Hemodilution by 6% Hetastarch in 0.9% Sodium Chloride Injection may also result in 24 hour declines of total protein, albumin, calcium, and fibrinogen levels. Regular and frequent clinical evaluation and complete blood counts (CBC) are necessary for proper monitoring of 6% Hetastarch in 0.9% Sodium Chloride Injection use during leukapheresis. If the frequency of leukapheresis is to exceed the guidelines for whole blood donation, you may wish to consider the following additional tests: total leukocyte and platelet counts, leukocyte differential count, hemoglobin and hematocrit, prothrombin time (PT), and partial thromboplastin time (PTT).

5.3 Hypersensitivity Reactions

Life threatening anaphylactic/anaphylactoid reactions including death have been rarely reported with 6% Hetastarch in 0.9% Sodium Chloride Injection. Patients may develop hypersensitivity reaction to corn starch from which this product is made. If a hypersensitivity reaction occurs, administration of the drug should be discontinued immediately and the appropriate treatment and supportive measures should be undertaken until symptoms have resolved.

5.4 Circulatory Overload

6% Hetastarch in 0.9% Sodium Chloride Injection has not been adequately evaluated to establish its safety in situations other than treatment of hypovolemia in elective surgery.

Large volumes of 6% Hetastarch in 0.9% Sodium Chloride Injection may transiently alter the coagulation mechanism due to hemodilution and a direct inhibitory action on Factor VIII. Administration of volumes of 6% Hetastarch in 0.9% Sodium Chloride Injection that are greater than 25% of the blood volume in less than 24 hours may cause significant hemodilution reflected by lower hematocrit and plasma protein values. Administration of packed red cells, platelets, or fresh frozen plasma should be considered if clinically indicated.

When using 6% Hetastarch in 0.9% Sodium Chloride Injection for plasma volume expansion, caution should be taken to avoid excessive hemodilution and circulatory overload especially in those patients at risk for developing congestive heart failure and pulmonary edema. 6% Hetastarch in 0.9% Sodium Chloride Injection is primarily excreted via the kidneys so caution should be exercised in patients who have impaired renal function. Although the risk of circulatory overload is largely dependent on the clinical circumstances, use of doses higher than 20 mL/kg/24h will increase the risk significantly. Increased risk of coagulation abnormalities and bleeding is also associated with higher doses. Monitor patients' vital signs and hemoglobin, hematocrit, platelet count, prothrombin time and partial thromboplastin time.

5.5 Liver Function Test

- Monitor liver function in patients receiving HES products, including 6% Hetastarch in 0.9% Sodium Chloride Injection

5.6 Drug/Laboratory Test Interactions

Bilirubin Levels

Indirect bilirubin levels of 8.3 mg/L (normal 0.0-7.0 mg/L) have been reported in 2 out of 20 normal subjects who received multiple infusions of 6% Hetastarch in 0.9% Sodium Chloride Injection. Total bilirubin was within normal limits at all times; indirect bilirubin returned to normal by 96 hours following the final infusion. The significance, if any, of these elevations is not known; however, caution should be observed before administering 6% Hetastarch in 0.9% Sodium Chloride Injection to patients with a history of liver disease.

Serum Amylase Levels

Elevated serum amylase levels may be observed temporarily following administration of 6% Hetastarch in 0.9% Sodium Chloride Injection although no association with pancreatitis has been demonstrated. Serum amylase levels cannot be used to assess or to evaluate for pancreatitis for 3-5 days after administration of 6% Hetastarch in 0.9% Sodium Chloride Injection. Elevated serum amylase levels persist for longer periods of time in patients with renal impairment. Hetastarch has not been shown to increase serum lipase.

Hemodialysis

6% Hetastarch in 0.9% Sodium Chloride Injection is not eliminated by hemodialysis. The utility of other extracorporeal elimination techniques has not been evaluated.

6 ADVERSE REACTIONS

Serious adverse reactions reported in postmarket clinical trials include increased mortality and AKI (including need for RRT) in critically ill subjects, including subjects with sepsis, and surgical subjects. Clinical trials have also shown increased mortality and AKI in blunt trauma subjects. Increased coagulopathy was reported in surgical subjects.

Most common adverse reactions are hypersensitivity, coagulopathy, hemodilution, circulatory overload and metabolic acidosis.

6.1 Clinical Trials Experience

Because clinical trials are conducted under widely varying conditions, adverse reaction rates observed in the clinical trials of a drug cannot be directly compared to rates in the clinical trials of another drug and may not reflect the rates observed in practice.

(Note: All of the studies listed below used licensed HES products except for reference 4.)

A randomized controlled trial (N=804) in severe sepsis patients using HES product (not approved in the U.S.) reported increased mortality (relative risk, 1.17; 95% CI, 1.01 to 1.36; p=0.03) and RRT (relative risk, 1.35; 95% CI, 1.01 to 1.80; p=0.04) in the HES treatment arm.^4

Another randomized controlled trial (N=196) using different HES in severe sepsis patients reported no difference in mortality (relative risk, 1.20; 95% CI, 0.83 to 1.74; p=0.33) and a trend for RRT (relative risk, 1.83; 95% CI, 0.93 to 3.59; p=0.06) in HES patients.^5

A randomized controlled trial (N=7000) using different HES in a heterogeneous patient population consisting of critically ill adult patients admitted to the ICU reported no difference in mortality (relative risk, 1.06; 95% CI, 0.96 to 1.18; p=0.26) but increased use of RRT (relative risk, 1.21; 95% CI, 1.00 to 1.45; p=0.04) in HES patients.^6

In a retrospective study of adult patients (N=1442) undergoing pulmonary or esophageal surgery who were prophylactically fluid restricted during the procedure, 74 developed AKI (5.1%) within the first 72 hours postoperatively. Fluid restriction neither increased nor was a risk factor for AKI. AKI occurred more often when HES products were administered to patients with decreased renal function or having >2 risk factors with normal renal function, whereas restriction of crystalloid was unrelated to AKI, regardless of preoperative renal function.^12

In a retrospective case series of high-risk adult vascular surgery patients (N=796) receiving fluid therapy during a vascular surgery procedure, logistic regression analysis using prespecified confounding variables or suspected risk factors for AKI showed that intraoperative administration of an HES product was associated with increased likelihood of 30-day mortality and need for RRT, compared with use of crystalloids alone.^13

In a retrospective study of adult subjects undergoing elective noncardiac surgery, patients (N=14,680) receiving an HES product and crystalloid were propensity-matched with patients (N=14,680) receiving only crystalloid. After controlling for potential confounding variables, odds of experiencing AKI of severe intensity with HES was 21% greater than with crystalloid alone. In addition, AKI risk increased as a function of HES volume.^14

In a prospective observational study assessing the impact of HES products on recipient renal graft outcomes in brain-dead organ donors, data were obtained on 986 kidneys transplanted from 529 donors. Kidneys from donors who received HES had a higher rate of delayed graft function in recipient subjects (41% versus 31%). After accounting for the propensity of donors to receive HES products, HES product administration was independently associated with an increased risk of delayed graft function in recipients. A dose response relationship also was evident.^15

In a randomized, controlled trial of adult subjects (N=33) undergoing elective cystectomy comparing an HES product versus lactated Ringer's, administration of HES reduced clot strength (Maximum Amplitude; p<0.001) and increased blinded evaluation of perioperative blood loss by more than 50% (2181 mL versus 1370 mL, respectively; p=0.04). There was no significant between-group difference with respect to frequency of reoperation or length of hospital stay.^16

In a prospective, sequential, observational study in adult subjects undergoing open heart surgery in association with cardiopulmonary bypass, fluid therapy using only an HES product (2004–2006, N=2137), 4% gelatin (2006–2008, N=2324) and crystalloids (N=2017, 2008–2010) led to increased need for renal replacement therapy after HES and gelatin, compared with crystalloid. Propensity score stratification confirmed greater use of RRT in the HES and gelatin periods compared to the crystalloid period. Fluid intake was higher in the crystalloid group only during the first 20 hours.^17

In a retrospective observational study, 606 adult patients underwent open heart surgery in association with cardiopulmonary bypass. Until July 2013 they received an HES product (N=247) both as pump prime (1500 mL) and intraoperative fluid replacement (1000 mL), but only crystalloid (N=359) from August 2013 onward. The frequency (percent) of postoperative AKI was higher in patients receiving HES (N=53; 21.5%) than those receiving crystalloid (N=34; 9.5%). Surgical revision for rebleeding also was higher for HES (N=11; 4.6%) than for crystalloid (N=5; 1.4%).^18

In a meta-analysis of RCTs (n=15) in adult subjects (N=4409) undergoing surgery who received an HES product, significantly more HES subjects (83/2157; 3.8%) than controls (56/2252; 2.5%) underwent RRT (relative risk, 1.44; 95% CI, 1.04, 2.01).^19

In a retrospective observational study of adult blunt and penetrating trauma patients, use of an HES product was a significant independent predictor of AKI after blunt trauma, but not penetrating trauma, in multiple logistic regression analysis. In separate logistic regression models, HES also was a significant predictor of mortality after blunt trauma but not penetrating trauma.^20

In a retrospective observational study of severely injured adult blunt (89%) and penetrating (11%) trauma patients (N=413) admitted to the ICU, 103 patients developed AKI within the first week of ICU admission. AKI was associated with increased 30-day (17.5% versus 5.8%, AKI versus non-AKI cohorts, respectively) and 1-year mortality (26.2% versus 7.1%). Univariate and multivariable regression analyses of prespecified risk factors for AKI found that volume loading using an HES product was independently associated with postinjury AKI within the first 24 hours.^21

6.2 Postmarketing Experience

Because adverse reactions are reported voluntarily post-approval from a population of uncertain size, it is not always possible to reliably estimate the frequency of these reactions or establish a causal relationship to product exposure.

The following adverse reactions have been identified and reported during the post-approval use of HES products:

Hypersensitivity reactions

including death, life-threatening anaphylactic/anaphylactoid reactions, cardiac arrest, ventricular fibrillation, severe hypotension, non-cardiac pulmonary edema, laryngeal edema, bronchospasm, angioedema, wheezing, restlessness, tachypnea, stridor, fever, chest pain, bradycardia, tachycardia, shortness of breath, chills, urticaria, pruritus, facial and periorbital edema, coughing, sneezing, flushing, erythema multiforme, and rash [see Warnings and Precautions (5.3)].

Cardiovascular reactions

including circulatory overload, congestive heart failure, and pulmonary edema [see Warnings and Precautions (5.4)].

Hematologic reactions

including intracranial bleeding, bleeding and/or anemia due to hemodilution [see Warnings and Precautions (5.4)] and/or Factor VIII deficiency, acquired von Willebrand's-like syndrome, and coagulopathy including rare cases of disseminated intravascular coagulopathy and hemolysis.

Metabolic reactions

including metabolic acidosis.

Other reactions

including vomiting, peripheral edema of the lower extremities, submaxillary and parotid glandular enlargement, mild influenza-like symptoms, headaches, and muscle pains. Hydroxyethyl starch-associated pruritus has been reported in some patients with deposits of hydroxyethyl starch in peripheral nerves.

7 DRUG INTERACTIONS

6% Hetastarch in 0.9% Sodium Chloride Injection should be used with caution in patients who have been anticoagulated with other drugs that negatively influence the coagulation system.

- The safety and compatibility of other additives have not been established.

8 USE IN SPECIFIC POPULATIONS

8.1 Pregnancy

Hetastarch has been shown to have an embryocidal effect on New Zealand rabbits when given intravenously over the entire organogenesis period in a daily dose 1/2 times the maximum recommended therapeutic human dose (1500 mL) and on BD rats when given intraperitoneally, from the 16th to the 21st day of pregnancy, in a daily dose 2.3 times the maximum recommended therapeutic human dose. When hetastarch was administered to New Zealand rabbits, BD rats, and swiss mice with intravenous daily doses of 2 times, 1/3 times, and 1 times the maximum recommended therapeutic human dose respectively over several days during the period of gestation, no evidence of teratogenicity was evident.

There are no adequate and well-controlled studies in pregnant women. 6% Hetastarch in 0.9% Sodium Chloride Injection should be used during pregnancy only if the potential benefit justifies the potential risk to the fetus.

8.3 Nursing Mothers

It is not known whether hetastarch is excreted in human milk. Because many drugs are excreted in human milk, caution should be exercised when 6% Hetastarch in 0.9% Sodium Chloride Injection is administered to a nursing woman.

8.4 Pediatric Use

The safety and effectiveness of hetastarch in pediatric patients have not been established. Adequate, well-controlled clinical trials to establish the safety and effectiveness of 6% Hetastarch in 0.9% Sodium Chloride Injection in pediatric patients have not been conducted.

11 DESCRIPTION

6% Hetastarch in 0.9% Sodium Chloride Injection is a sterile, nonpyrogenic solution for intravenous administration.

Each 100 mL contains:
Hetastarch............................................................................ 6 g
Sodium Chloride, USP........................................................ 0.9 g
Water for Injection, USP..................................................... qs
pH adjusted with Sodium Hydroxide, NF if necessary
Concentration of Electrolytes (mEq/L): Sodium (Na^+) 154, Chloride (Cl^-) 154 (not including ions for pH adjustment).
pH: 5.5 (3.5 to 7.0)
Total osmolar concentration is 308 mOsmol/liter (calc).

Hetastarch is a synthetic colloid derived from a waxy starch composed almost entirely of amylopectin. Hydroxyethyl ether groups are introduced into the glucose units of the starch, and the resultant material is hydrolyzed to yield a product with a molecular weight suitable for use as a plasma volume expander and erythrocyte sedimenting agent. The molar substitution is approximately 0.75 which means hetastarch has an average of approximately 75 hydroxyethyl groups for every 100 glucose units. The weight average molecular weight is approximately 670,000 with a range of 550,000 to 800,000 and with at least 80% of the polymers falling within the range of 20,000 to 2,500,000. Hydroxyethyl groups are attached by ether linkage primarily at C-2 of the glucose unit and to a lesser extent at C-3 and C-6. The polymer resembles glycogen, and the polymerized D-glucose units are joined primarily by α-1,4 linkages with occasional α-1,6 branching linkages. The degree of branching is approximately 1:20 which means that there is one 1–6 branch for every 20 glucose monomer units.

The chemical name for hetastarch is hydroxyethyl starch.

The structural formula is as follows:

Amylopectin derivative in which R2, R3, and R6 are H or CH2CH2OH, or R6 is a branching point in the starch polymer connected through a 1-6 linkage to additional alpha-D-glucopyranosyl units.

Hetastarch is an artificial colloid pharmacologically classified as a plasma volume expander; 0.9% Sodium Chloride Injection is a fluid and electrolyte replenisher.

6% Hetastarch in 0.9% Sodium Chloride Injection is a clear, pale yellow to amber solution. Exposure to prolonged adverse storage conditions may result in a change to a turbid deep brown or the formation of a crystalline precipitate. Do not use the solution if these conditions are evident.

The flexible plastic container is fabricated from a specially formulated polyvinylchloride. Water can permeate from inside the container into the overwrap but not in amounts sufficient to affect the solution significantly.

Solutions in contact with the plastic container may leach out certain chemical components from the plastic in very small amounts; however, biological testing was supportive of the safety of the plastic container materials.

Exposure to temperatures above 25°C/77°F during transport and storage will lead to minor losses in moisture content. Higher temperatures lead to greater losses. It is unlikely that these minor losses will lead to clinically significant changes within the expiration period.

12 CLINICAL PHARMACOLOGY

12.1 Mechanism of Action

The plasma volume expansion produced by 6% Hetastarch in 0.9% Sodium Chloride Injection approximates that of 5% Albumin (Human). Intravenous infusion of 6% Hetastarch in 0.9% Sodium Chloride Injection results in expansion of plasma volume.

12.2 Pharmacodynamics

6% Hetastarch in 0.9% Sodium Chloride Injection results in expansion of plasma volume that decreases over the succeeding 24 to 36 hours. The degree of plasma volume expansion and improvement in hemodynamic state depend upon the patient's intravascular status.

12.3 Pharmacokinetics

Hetastarch molecules below 50,000 molecular weight are rapidly eliminated by renal excretion. A single dose of approximately 500 mL of 6% Hetastarch in 0.9% Sodium Chloride Injection (approximately 30 g) results in elimination in the urine of approximately 33% of the dose within 24 hours. This is a variable process but generally results in an intravascular hetastarch concentration of less than 10% of the total dose injected by two weeks. A study of the biliary excretion of 6% Hetastarch in 0.9% Sodium Chloride Injection in 10 healthy males accounted for less than 1% of the dose over a 14 day period. The hydroxyethyl group is not cleaved by the body but remains intact and attached to glucose units when excreted. Significant quantities of glucose are not produced as hydroxyethylation prevents complete metabolism of the smaller polymers.

The addition of hetastarch to whole blood increases the erythrocyte sedimentation rate. Therefore, 6% Hetastarch in 0.9% Sodium Chloride Injection is used to improve the efficiency of granulocyte collection by centrifugal means.

13 NONCLINICAL TOXICOLOGY

13.1 Carcinogenesis, Mutagenesis, Impairment of Fertility

Long-term studies of animals have not been performed to evaluate the carcinogenic potential of hetastarch.

14 CLINICAL STUDIES

Surgical Patients Comparative Studies

In randomized, controlled, comparative studies of 6% Hetastarch in 0.9% Sodium Chloride Injection (n=92) and Albumin (n=85) in surgical patients, no patient in either treatment group had a bleeding complication and no significant difference was found in the amount of blood loss between the treatment groups.^7-10

Pediatric Postoperative Volume Expander Study

In one small double-blind study, 47 infants, children, and adolescents (ages 1 year to 15.5 years) scheduled for repair of congenital heart disease with moderate hypothermia were randomized to receive either 6% Hetastarch in 0.9% Sodium Chloride Injection or Albumin as a postoperative volume expander during the first 24 hours after surgery. Thirty-eight children required colloid replacement therapy, of which 20 children received 6% Hetastarch in 0.9% Sodium Chloride Injection. No differences were found in the coagulation parameters or in the amount of replacement fluids required in the children receiving 20 mL/kg or less of either colloid replacement therapy. In children who received greater than 20 mL/kg of 6% Hetastarch in 0.9% Sodium Chloride Injection, an increase in prothrombin time was demonstrated (p=0.006).^11 There were no neonates included in this study [see Use in Specific Populations (8.4)].

Adult Critically Ill Studies

Three randomized controlled trials (RCTs) followed critically ill adult patients treated with different HES products for 90 days.

One trial (N=804) in severe sepsis patients using HES product (not approved in the U.S.) reported increased mortality (relative risk, 1.17; 95% CI, 1.01 to 1.36; p=0.03) and RRT (relative risk, 1.35; 95% CI, 1.01 to 1.80; p=0.04) in the HES treatment arm.^4

Another trial (N=196) using different HES in severe sepsis patients reported no difference in mortality (relative risk,1.20; 95% CI, 0.83 to 1.74; p=0.33) and a trend for RRT (relative risk, 1.83; 95% CI, 0.93 to 3.59; p=0.06) in HES patients.^5

A third trial (N=7000) using different HES in a heterogeneous patient population consisting of critically ill adult patients admitted to the ICU reported no difference in mortality (relative risk, 1.06; 95% CI, 0.96 to 1.18; p=0.26) but increased use of RRT (relative risk, 1.21; 95% CI, 1.00 to 1.45; p=0.04) in HES patients.^6

15 REFERENCES

1. Knutson JE., et al., Does Intraoperative Hetastarch Administration Increase Blood Loss and Transfusion Requirements After Cardiac Surgery? Anesthesia Analg., 2000;90:801–7.
2. Cope JT., et al., Intraoperative Hetastarch Infusion Impairs Hemostasis After Cardiac Operations. The Annals of Thoracic Surgery, 1997;63:78–83.
3. Damon L., Intracranial Bleeding During Treatment with Hydroxyethyl Starch. New England Journal of Medicine, 1987;317(15):964–965.
4. Perner A, et al., Hydroxyethyl starch 130/0.42 versus Ringer's acetate in severe sepsis patients. The New England Journal of Medicine, 2012 July 12;367(2):124–34.
5. Guidet B, et al., Assessment of hemodynamic efficacy and safety of 6% hydroxyethyl starch 130/0.4 vs 0.9% NaCl fluid replacement in patients with severe sepsis: The CRYSTMAS Study. Critical Care, 2012 May 24;16(3):R94.
6. Myburgh JA, et al., Hydroxyethyl starch or saline for fluid resuscitation in intensive care. The New England Journal of Medicine, 2012 November 15;367(20):1901–11.
7. Diehl J., et al., Clinical Comparison of Hetastarch and Albumin in Postoperative Cardiac Patients. The Annals of Thoracic Surgery, 1982;34(6):674–679.
8. Gold M., et al., Comparison of Hetastarch to Albumin for Perioperative Bleeding in Patients Undergoing Abdominal Aortic Aneurysm Surgery. Annals of Surgery, 1990;211(4):482–485.
9. Kirklin J., et al., Hydroxyethyl Starch versus Albumin for Colloid Infusion Following Cardiopulmonary Bypass in Patients Undergoing Myocardial Revascularization. The Annals of Thoracic Surgery, 1984;37(1):40–46.
10. Moggio RA., et al., Hemodynamic Comparison of Albumin and Hydroxyethyl Starch in Postoperative Cardiac Surgery Patients. Critical Care Medicine, 1983;11(12):943–945.
11. Brutocao D., et al., Comparison of Hetastarch with Albumin for Postoperative Volume Expansion in Children After Cardiopulmonary Bypass. Journal of Cardiothoracic and Vascular Anesthesia, 1996;10(3):348–351.
12. Ahn HJ, Kim JA, Lee AR, et al. The risk of acute kidney injury from fluid restriction and hydroxyethyl starch in thoracic surgery. Anesth Analg 2016; 122(1):186–193.
13. Green RS, Butler MB, Hicks SD, et al. Effect of hydroxyethyl starch on outcomes in high-risk vascular surgery patients: A retrospective analysis. J Cardiothorac Vasc Anesth 2016; 30(4):967–72.
14. Kashy BK, Podolyak A, Makarova N, et al. Effect of hydroxyethyl starch on postoperative kidney function in patients having noncardiac surgery. Anesthesiology 2014; 121 (4):730–9.
15. Patel MS, Niemann CU, Sally MB, et al. The impact of hydroxyethyl starch use in deceased organ donors on the development of delayed graft function in kidney transplant recipients: A Propensity-Adjusted Analysis. Am J of Transplant 2015; 15 (8):2152–8.
16. Rasmussen KC, Johansson PI, Højskov M, et al. Hydroxyethyl starch reduces coagulation competence and increases blood loss during major surgery: results from a randomized controlled trial. Ann Surg 2014; 259 (2):249–54.
17. Bayer O, Schwarzkopf D, Doenst T, et al. Perioperative fluid therapy with tetrastarch and gelatin in cardiac surgery — a prospective sequential analysis. Crit Care Med 2013; 41(11):2532–42.
18. Lagny MG, Roediger L, Koch JN, et al. Hydroxyethyl starch 130/0.4 and the risk of acute kidney injury after cardiopulmonary bypass: A single-center retrospective study. J of Cardiothorac and Vasc Anesth 2016: 30(4):869–75.
19. Wilkes MM, Navickis RJ. Postoperative renal replacement therapy after hydroxyethyl starch infusion: a meta-analysis of randomized trials. Neth J Crit Care 2014; 18:4–9.
20. Allen CJ, Valle EJ, Jouria JM, et al. Differences between blunt and penetrating trauma after resuscitation with HES. J Trauma Acute Care Surg 2014; 77(6):859–64.
21. Eriksson M, Brattström O, Mårtensson J, et al. Acute kidney injury following severe trauma: Risk factors and long-term outcome. J Trauma Acute Care Surg 2015; 79(3):407–12.

16 HOW SUPPLIED/STORAGE AND HANDLING

6% Hetastarch in 0.9% Sodium Chloride Injection is supplied sterile and nonpyrogenic in 500 mL single-dose flexible plastic containers.

Unit of Sale | Concentration
NDC 0409-7248-03; Case containing 12 Flexible Plastic Containers | 30 g Hetastarch/500 mL; (6 g Hetastarch/100 mL)

Exposure of pharmaceutical products to heat should be minimized. Avoid excessive heat. Protect from freezing.

Store at 20 to 25°C (68 to 77°F). [See USP Controlled Room Temperature.]

Rx only

Distributed by Hospira, Inc., Lake Forest, IL 60045 USA

LAB-1287-6.0

PRINCIPAL DISPLAY PANEL - 500 mL Bag

500 mL
NDC 0409-7248-13

6% HETASTARCH
in 0.9% Sodium Chloride Injection
For intravenous use only

EACH 100 mL CONTAINS HETASTARCH, 6 g AND SODIUM
CHLORIDE 0.9 g IN WATER FOR INJECTION. MAY CONTAIN
SODIUM HYDROXIDE FOR pH ADJUSTMENT. ELECTROLYTES
(mEq/L): SODIUM 154, CHLORIDE 154. 308 mOsmol/LITER
(calc). pH 5.5 (3.5 TO 7.0).
IF ADMINISTRATION IS BY PRESSURE INFUSION, ALL AIR
SHOULD BE WITHDRAWN OR EXPELLED FROM THE BAG
THROUGH THE MEDICATION PORT PRIOR TO INFUSION.
STERILE, NONPYROGENIC. SINGLE-DOSE CONTAINER.
DISCARD UNUSED PORTION. USE ONLY IF SOLUTION IS
CLEAR. USUAL DOSAGE: SEE INSERT. STORE AT 20 TO 25°C
(68 TO 77°F). [SEE USP CONTROLLED ROOM TEMPERATURE.]
PROTECT FROM FREEZING. SEE INSERT.
DO NOT INTRODUCE ADDITIVES INTO THIS CONTAINER

Rx ONLY

3
V
CONTAINS DEHP

DISTRIBUTED BY HOSPIRA, INC.,
LAKE FOREST, IL 60045 USA

Hospira

IM-4487
14477801

PRINCIPAL DISPLAY PANEL - 500 mL Bag Overwrap

2
HDPE

TO OPEN TEAR AT NOTCH

DO NOT REMOVE FROM OVERWRAP UNTIL READY FOR USE. AFTER REMOVING
THE OVERWRAP, CHECK FOR MINUTE LEAKS BY SQUEEZING CONTAINER
FIRMLY. IF LEAKS ARE FOUND, DISCARD SOLUTION AS STERILITY MAY BE
IMPAIRED. RECOMMENDED STORAGE: ROOM TEMPERATURE (25°C). AVOID
EXCESSIVE HEAT. PROTECT FROM FREEZING. SEE INSERT.
IM-4498

Not Made With Natural Rubber Latex

14622100